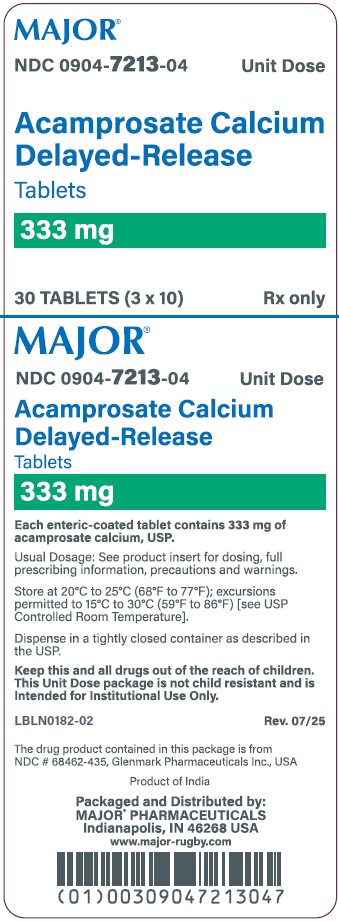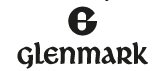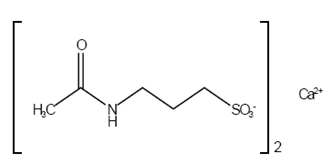 DRUG LABEL: Acamprosate Calcium
NDC: 0904-7213 | Form: TABLET, DELAYED RELEASE
Manufacturer: Major Pharmaceuticals
Category: prescription | Type: HUMAN PRESCRIPTION DRUG LABEL
Date: 20260211

ACTIVE INGREDIENTS: ACAMPROSATE CALCIUM 333 mg/1 1
INACTIVE INGREDIENTS: SILICON DIOXIDE; CROSPOVIDONE, UNSPECIFIED; METHACRYLIC ACID AND ETHYL ACRYLATE COPOLYMER; MAGNESIUM SILICATE; MAGNESIUM STEARATE; MICROCRYSTALLINE CELLULOSE; PROPYLENE GLYCOL; SODIUM STARCH GLYCOLATE TYPE A POTATO; TALC; POVIDONE, UNSPECIFIED

HIGHLIGHTS OF PRESCRIBING INFORMATION

These highlights do not include all the information needed to use ACAMPROSATE CALCIUM DELAYED-RELEASE TABLETS safely and effectively. See full prescribing information for ACAMPROSATE CALCIUM DELAYED-RELEASE TABLETS.
ACAMPROSATE CALCIUM delayed-release tablets, for oral use
Initial U.S. Approval: 2004

1 INDICATIONS AND USAGE

- Acamprosate calcium delayed-release tablets are indicated for the maintenance of abstinence from alcohol in patients with alcohol dependence who are abstinent at treatment initiation (1, 14).
- Treatment with acamprosate calcium delayed-release tablets should be part of a comprehensive management program that includes psychosocial support (1).

2 DOSAGE AND ADMINISTRATION

- Recommended dose: 666 mg (two 333 mg tablets) taken three times daily (2).
- Dose reduction to one 333 mg tablet taken three times daily for patients with moderate renal impairment (creatinine clearance 30 to 50 mL/min) (2.1).
- Acamprosate calcium delayed-release tablets are contraindicated in patients with severe renal impairment (creatinine clearance of ≤30 mL/min) (2.1, 4.2, 5.1, 8.6, 12.3).

3 DOSAGE FORMS AND STRENGTHS

Enteric-coated tablets, 333 mg (3).

4 CONTRAINDICATIONS

- Acamprosate calcium is contraindicated in patients who previously have exhibited hypersensitivity to acamprosate calcium or any of its components (4.1).
- Acamprosate calcium is contraindicated in patients with severe renal impairment (4.2).

5 WARNINGS AND PRECAUTIONS

- Dose reduction is required for patients with moderate renal impairment (5.1).
- Monitor patients for depression or suicidal ideation and prompt patients, families, and caregivers to report such symptoms to the health care provider (5.2).

6 ADVERSE REACTIONS

Common adverse events that occurred in any acamprosate calcium treatment group at a rate of 3% or greater and greater than the placebo group in controlled clinical trials with spontaneously reported adverse events are: accidental injury, asthenia, pain, anorexia, diarrhea, flatulence, nausea, anxiety, depression, dizziness, dry mouth, insomnia, paresthesia, pruritus and sweating (6.1).

To report SUSPECTED ADVERSE REACTIONS, contact Glenmark Pharmaceuticals Inc., USA at 1 (888) 721-7115 or FDA at 1-800-FDA-1088 or www.fda.gov/medwatch.

8 USE IN SPECIFIC POPULATIONS

- Pregnancy: Acamprosate calcium should be used during pregnancy only if the potential benefit justifies the potential risk to the fetus (8.1).
- Nursing Mothers: Caution should be exercised when acamprosate calcium is administered to a nursing woman (8.3).
- Renal Impairment: Dose reduction required for moderate renal impairment; contraindicated in severe renal impairment (2.1, 4.2, 5.1, 8.6, 12.3)

FULL PRESCRIBING INFORMATION

1 INDICATIONS AND USAGE

Acamprosate calcium delayed-release tablets are indicated for the maintenance of abstinence from alcohol in patients with alcohol dependence who are abstinent at treatment initiation. Treatment with acamprosate calcium delayed-release tablets should be part of a comprehensive management program that includes psychosocial support.

The efficacy of acamprosate calcium delayed-release tablets in promoting abstinence has not been demonstrated in subjects who have not undergone detoxification and not achieved alcohol abstinence prior to beginning acamprosate calcium delayed-release tablets treatment. The efficacy of acamprosate calcium delayed-release tablets in promoting abstinence from alcohol in polysubstance abusers has not been adequately assessed.

2 DOSAGE AND ADMINISTRATION

The recommended dose of acamprosate calcium delayed-release tablets is two 333 mg tablets (each dose should total 666 mg) taken three times daily. A lower dose may be effective in some patients.

Although dosing may be done without regard to meals, dosing with meals was employed during clinical trials and is suggested in those patients who regularly eat three meals daily.

Treatment with acamprosate calcium delayed-release tablets should be initiated as soon as possible after the period of alcohol withdrawal, when the patient has achieved abstinence, and should be maintained if the patient relapses. Acamprosate calcium delayed-release tablets should be used as part of a comprehensive psychosocial treatment program.

2.1 Dosage in Renal Impairment

For patients with moderate renal impairment (creatinine clearance of 30 to 50 mL/min), a starting dose of one 333 mg tablet taken three times daily is recommended. Acamprosate calcium delayed-release tablets are contraindicated in patients with severe renal impairment (creatinine clearance of ≤30 mL/min) [see Contraindications (4.2), Warnings and Precautions (5.1), Use in Specific Populations (8.6), and Clinical Pharmacology (12.3)].

3 DOSAGE FORMS AND STRENGTHS

Acamprosate calcium delayed-release tablets, 333 mg are white to off-white, round, biconvex, enteric-coated tablets debossed with “435” on one side and plain on the other side.

4 CONTRAINDICATIONS

4.1 Hypersensitivity to Acamprosate Calcium

Acamprosate calcium is contraindicated in patients who previously have exhibited hypersensitivity to acamprosate calcium or any of its components.

4.2 Severe Renal Impairment

Acamprosate calcium is contraindicated in patients with severe renal impairment (creatinine clearance of ≤30 mL/min) [see Dosage and Administration (2.1), Warnings and Precautions (5.1), Use in Specific Populations (8.6), and Clinical Pharmacology (12.3)].

5 WARNINGS AND PRECAUTIONS

5.1 Renal Impairment

Treatment with acamprosate calcium in patients with moderate renal impairment (creatinine clearance of 30 to 50 mL/min) requires a dose reduction [see Dosage and Administration (2.1)]. Acamprosate calcium is contraindicated in patients with severe renal impairment (creatinine clearance of ≤30 mL/min) [see Dosage and Administration (2.1), Contraindications (4.2), Use in Specific Populations (8.6), and Clinical Pharmacology (12.3)].

5.2 Suicidality and Depression

In controlled clinical trials of acamprosate calcium, adverse events of a suicidal nature (suicidal ideation, suicide attempts, completed suicides) were infrequent overall, but were more common in acamprosate calcium-treated patients than in patients treated with placebo (1.4% vs. 0.5% in studies of 6 months or less; 2.4% vs. 0.8% in year-long studies). Completed suicides occurred in 3 of 2272 (0.13%) patients in the pooled acamprosate group from all controlled studies and 2 of 1962 patients (0.10%) in the placebo group. Adverse events coded as "depression" were reported at similar rates in acamprosate calcium-treated and placebo-treated patients. Although many of these events occurred in the context of alcohol relapse, and the interrelationship between alcohol dependence, depression and suicidality is well-recognized and complex, no consistent pattern of relationship between the clinical course of recovery from alcoholism and the emergence of suicidality was identified. Alcohol-dependent patients, including those patients being treated with acamprosate calcium, should be monitored for the development of symptoms of depression or suicidal thinking. Families and caregivers of patients being treated with acamprosate calcium should be alerted to the need to monitor patients for the emergence of symptoms of depression or suicidality, and to report such symptoms to the patient's health care provider.

5.3 Alcohol Withdrawal

Use of acamprosate calcium does not eliminate or diminish withdrawal symptoms.

6 ADVERSE REACTIONS

6.1 Clinical Trials Experience

Because clinical trials are conducted under widely varying conditions, adverse reaction rates observed in the clinical trials of a drug cannot be directly compared to rates in the clinical trials of another drug and may not reflect the rates observed in clinical practice.

Clinically significant serious adverse reactions associated with acamprosate calcium described elsewhere in labeling include suicidality and depression and acute kidney failure [see Warnings and Precautions (5.2), and Adverse Reactions (6.2)].

The adverse event data described below reflect the safety experience in over 7000 patients exposed to acamprosate calcium for up to one year, including over 2000 acamprosate calcium-exposed patients who participated in placebo-controlled trials.

Adverse Events Leading to Discontinuation

In placebo-controlled trials of 6 months or less, 8% of acamprosate calcium-treated patients discontinued treatment due to an adverse event, as compared to 6% of patients treated with placebo. In studies longer than 6 months, the discontinuation rate due to adverse events was 7% in both the placebo-treated and the acamprosate calcium-treated patients. Only diarrhea was associated with the discontinuation of more than 1% of patients (2% of acamprosate calcium-treated vs. 0.7% of placebo-treated patients). Other events, including nausea, depression, and anxiety, while accounting for discontinuation in less than 1% of patients, were nevertheless more commonly cited in association with discontinuation in acamprosate calcium-treated patients than in placebo-treated patients.

Common Adverse Events Reported in Controlled Trials

Common adverse events were collected spontaneously in some controlled studies and using a checklist in other studies. The overall profile of adverse events was similar using either method. Table 1 shows those events that occurred in any acamprosate calcium treatment group at a rate of 3% or greater and greater than the placebo group in controlled clinical trials with spontaneously reported adverse events. The reported frequencies of adverse events represent the proportion of individuals who experienced, at least once, a treatment-emergent adverse event of the type listed, without regard to the causal relationship of the events to the drug.

Table 1. Events Occurring at a Rate of at Least 3% and Greater than Placebo in any Acamprosate Calcium Treatment Group in Controlled Clinical Trials with Spontaneously Reported Adverse Events.

Body System/Preferred; Term | Number of Patients (%) with Events
Body System/Preferred; Term | Acamprosate Calcium 1332 mg/day | Acamprosate Calcium; 1998 mg/day^1 | Acamprosate Calcium Pooled^2 | Placebo
Number of patients in; Treatment Group | 397 | 1539 | 2019 | 1706
Number (%) of patients; with an AE | 248 (62%) | 910 (59%) | 1231 (61%) | 955 (56%)
Body as a Whole | 121 (30%) | 513 (33%) | 685 (34%) | 517 (30%)
Accidental Injury*† | 17 (4%) | 44 (3%) | 70 (3%) | 52 (3%)
Asthenia | 29 (7%) | 79 (5%) | 114 (6%) | 93 (5%)
Pain | 6 (2%) | 56 (4%) | 65 (3%) | 55 (3%)
Digestive System | 85 (21%) | 440 (29%) | 574 (28%) | 344 (20%)
Anorexia | 20 (5%) | 35 (2%) | 57 (3%) | 44 (3%)
Diarrhea | 39 (10%) | 257 (17%) | 329 (16%) | 166 (10%)
Flatulence | 4 (1%) | 55 (4%) | 63 (3%) | 28 (2%)
Nausea | 11 (3%) | 69 (4%) | 87 (4%) | 58 (3%)
Nervous System | 150 (38%) | 417 (27%) | 598 (30%) | 500 (29%)
Anxiety††** | 32 (8%) | 80 (5%) | 118 (6%) | 98 (6%)
Depression | 33 (8%) | 63 (4%) | 102 (5%) | 87 (5%)
Dizziness | 15 (4%) | 49 (3%) | 67 (3%) | 44 (3%)
Dry mouth | 13 (3%) | 23 (1%) | 36 (2%) | 28 (2%)
Insomnia | 34 (9%) | 94 (6%) | 137 (7%) | 121 (7%)
Paresthesia | 11 (3%) | 29 (2%) | 40 (2%) | 34 (2%)
Skin and Appendages | 26 (7%) | 150 (10%) | 187 (9%) | 169 (10%)
Pruritus | 12 (3%) | 68 (4%) | 82 (4%) | 58 (3%)
Sweating | 11 (3%) | 27 (2%) | 40 (2%) | 39 (2%)

†*includes events coded as “fracture” by sponsor;

††**includes events coded as “nervousness” by sponsor

^1 includes 258 patients treated with acamprosate calcium 2000 mg/day, using a different dosage strength and regimen.

^2 includes all patients in the first two columns as well as 83 patients treated with acamprosate calcium 3000 mg/day, using a different dosage strength and regimen.

Concomitant Therapies

In clinical trials, the safety profile in subjects treated with acamprosate calcium concomitantly with anxiolytics, hypnotics and sedatives (including benzodiazepines), or non-opioid analgesics was similar to that of subjects taking placebo with these concomitant medications. Patients taking acamprosate calcium concomitantly with antidepressants more commonly reported both weight gain and weight loss, compared with patients taking either medication alone.

Other Events Observed During the Premarketing Evaluation of Acamprosate Calcium

Following is a list of terms that reflect treatment-emergent adverse events reported by patients treated with acamprosate calcium in 20 clinical trials (4461 patients treated with acamprosate calcium, 3526 of whom received the maximum recommended dose of 1998 mg/day for up to one year in duration). This listing does not include those events already listed above; events for which a drug cause was considered remote; event terms which were so general as to be uninformative; and events reported only once which were not likely to be acutely life-threatening.

Events are further categorized by body system and listed in order of decreasing frequency according to the following definitions: frequent adverse events are those occurring in at least 1/100 patients (only those not already listed in the summary of adverse events in controlled trials appear in this listing); infrequent adverse events are those occurring in 1/100 to 1/1000 patients; rare events are those occurring in fewer than 1/1000 patients.

Body as a Whole – Frequent: headache, abdominal pain, back pain, infection, flu syndrome, chest pain, chills, suicide attempt; Infrequent: fever, intentional overdose, malaise, allergic reaction, abscess, neck pain, hernia, intentional injury; Rare: ascites, face edema, photosensitivity reaction, abdomen enlarged, sudden death.

Cardiovascular System – Frequent: palpitation, syncope; Infrequent: hypotension, tachycardia, hemorrhage, angina pectoris, migraine, varicose vein, myocardial infarct, phlebitis, postural hypotension; Rare: heart failure, mesenteric arterial occlusion, cardiomyopathy, deep thrombophlebitis, shock.

Digestive System – Frequent: vomiting, dyspepsia, constipation, increased appetite; Infrequent: liver function tests abnormal, gastroenteritis, gastritis, dysphagia, eructation, gastrointestinal hemorrhage, pancreatitis, rectal hemorrhage, liver cirrhosis, esophagitis, hematemesis, nausea and vomiting, hepatitis; Rare: melena, stomach ulcer, cholecystitis, colitis, duodenal ulcer, mouth ulceration, carcinoma of liver.

Endocrine System – Rare: goiter, hypothyroidism.

Hemic and Lymphatic System – Infrequent: anemia, ecchymosis, eosinophilia, lymphocytosis, thrombocytopenia; Rare: leukopenia, lymphadenopathy, monocytosis.

Metabolic and Nutritional Disorders – Frequent – peripheral edema, weight gain; Infrequent: weight loss, hyperglycemia, SGOT increased, SGPT increased, gout, thirst, hyperuricemia, diabetes mellitus, avitaminosis, bilirubinemia; Rare: alkaline phosphatase increased, creatinine increased, hyponatremia, lactic dehydrogenase increased.

Musculoskeletal System – Frequent – myalgia, arthralgia; Infrequent: leg cramps; Rare: rheumatoid arthritis, myopathy.

Nervous System – Frequent –somnolence, libido decreased, amnesia, thinking abnormal, tremor, vasodilatation, hypertension; Infrequent: convulsion, confusion, libido increased, vertigo, withdrawal syndrome, apathy, suicidal ideation, neuralgia, hostility, agitation, neurosis, abnormal dreams, hallucinations, hypesthesia; Rare: alcohol craving, psychosis, hyperkinesia, twitching, depersonalization, increased salivation, paranoid reaction, torticollis, encephalopathy, manic reaction.

Respiratory System – Frequent: rhinitis, cough increased, dyspnea, pharyngitis, bronchitis; Infrequent: asthma, epistaxis, pneumonia; Rare: laryngismus, pulmonary embolus.

Skin and Appendages – Frequent: rash; Infrequent: acne, eczema, alopecia, maculopapular rash, dry skin, urticaria, exfoliative dermatitis, vesiculobullous rash; Rare: psoriasis.

Special Senses – Frequent: abnormal vision, taste perversion; Infrequent: tinnitus, amblyopia, deafness; Rare: ophthalmitis, diplopia, photophobia.

Urogenital System – Frequent: impotence; Infrequent – metrorrhagia, urinary frequency, urinary tract infection, sexual function abnormal, urinary incontinence, vaginitis; Rare: kidney calculus, abnormal ejaculation, hematuria, menorrhagia, nocturia, polyuria, urinary urgency.

6.2 Postmarketing Experience

The following adverse reactions have been identified during post approval use of acamprosate calcium. Because these reactions are reported voluntarily from a population of uncertain size, it is not always possible to reliably estimate their frequency or establish a causal relationship to drug exposure.

Serious Adverse Events Observed During the Non-US Postmarketing Evaluation of Acamprosate Calcium

The serious adverse event of acute kidney failure has been reported to be temporally associated with acamprosate calcium treatment in at least 3 patients and is not described elsewhere in the labeling.

7 DRUG INTERACTIONS

Acamprosate does not affect the pharmacokinetics of alcohol. The pharmacokinetics of acamprosate are not affected by alcohol, diazepam, or disulfiram, and clinically important interactions between naltrexone and acamprosate were not observed [see Clinical Pharmacology (12.3)].

8 USE IN SPECIFIC POPULATIONS

8.1 Pregnancy

Teratogenic effects: Acamprosate calcium has been shown to be teratogenic in rats when given in doses that are approximately equal to the human dose (on a mg/m^2 basis) and in rabbits when given in doses that are approximately 3 times the human dose (on a mg/m^2 basis). Acamprosate calcium produced a dose-related increase in the number of fetuses with malformations in rats at oral doses of 300 mg/kg/day or greater (approximately equal to the maximum recommended human daily (MRHD) oral dose on a mg/m^2 basis). The malformations included hydronephrosis, malformed iris, retinal dysplasia, and retroesophageal subclavian artery. No findings were observed at an oral dose of 50 mg/kg/day (approximately one-fifth the MRHD oral dose on a mg/m^2 basis). An increased incidence of hydronephrosis was also noted in Burgundy Tawny rabbits at oral doses of 400 mg/kg/day or greater (approximately 3 times the MRHD oral dose on a mg/m^2 basis). No developmental effects were observed in New Zealand white rabbits at oral doses up to 1000 mg/kg/day (approximately 8 times the MRHD oral dose on a mg/m^2 basis). The findings in animals should be considered in relation to known adverse developmental effects of ethyl alcohol, which include the characteristics of fetal alcohol syndrome (craniofacial dysmorphism, intrauterine and postnatal growth retardation, retarded psychomotor and intellectual development) and milder forms of neurological and behavioral disorders in humans. There are no adequate and well controlled studies in pregnant women. Acamprosate calcium should be used during pregnancy only if the potential benefit justifies the potential risk to the fetus.

Nonteratogenic effects: A study conducted in pregnant mice that were administered acamprosate calcium by the oral route starting on Day 15 of gestation through the end of lactation on postnatal day 28 demonstrated an increased incidence of still-born fetuses at doses of 960 mg/kg/day or greater (approximately 2 times the MRHD oral dose on a mg/m^2 basis). No effects were observed at a dose of 320 mg/kg/day (approximately one-half the MRHD dose on a mg/m2 basis).

8.2 Labor and Delivery

The potential for acamprosate calcium to affect the duration of labor and delivery is unknown.

8.3 Nursing Mothers

In animal studies, acamprosate was excreted in the milk of lactating rats dosed orally with acamprosate calcium. The concentration of acamprosate in milk compared to blood was 1.3:1. It is not known whether acamprosate is excreted in human milk. Because many drugs are excreted in human milk, caution should be exercised when acamprosate calcium is administered to a nursing woman.

8.4 Pediatric Use

The safety and efficacy of acamprosate calcium have not been established in the pediatric population.

8.5 Geriatric Use

Forty-one of the 4234 patients in double-blind, placebo-controlled, clinical trials of acamprosate calcium were 65 years of age or older, while none were 75 years of age or over. There were too few patients in the ≥65 age group to evaluate any differences in safety or effectiveness for geriatric patients compared to younger patients.

This drug is known to be substantially excreted by the kidney, and the risk of toxic reactions to this drug may be greater in patients with impaired renal function. Because elderly patients are more likely to have decreased renal function, care should be taken in dose selection, and it may be useful to monitor renal function [see Clinical Pharmacology (12.3), Adverse Reactions (6.1), and Dosage and Administration (2.1)].

8.6 Renal Impairment

Acamprosate calcium is contraindicated in patients with severe renal impairment (creatinine clearance of ≤30 mL/min) [see Dosage and Administration (2.1), Contraindications (4.2), Warnings and Precautions (5.1), and Clinical Pharmacology (12.3)].

10 OVERDOSAGE

In all reported cases of acute overdosage with acamprosate calcium (total reported doses of up to 56 grams of acamprosate calcium), the only symptom that could be reasonably associated with acamprosate calcium was diarrhea. Hypercalcemia has not been reported in cases of acute overdose. A risk of hypercalcemia should be considered in chronic overdosage only. Treatment of overdose should be symptomatic and supportive.

11 DESCRIPTION

Acamprosate calcium delayed-release tablets are supplied as an enteric-coated tablet for oral administration. Acamprosate calcium, USP is a synthetic compound with a chemical structure similar to that of the endogenous amino acid homotaurine, which is a structural analogue of the amino acid neurotransmitter γ-aminobutyric acid and the amino acid neuromodulator taurine. Its chemical name is calcium bis [3-(acetylamino) propane-1-sulfonate]. Its chemical formula is C10H20CaN2O8S2 and molecular weight is 400.5 g/mol. Its structural formula is:

Acamprosate calcium, USP is a white to almost white powder, odorless or nearly odorless powder. It is freely soluble in water and practically insoluble in alcohol and methylene chloride.

Each acamprosate calcium delayed-release tablet contains acamprosate calcium, USP 333 mg, equivalent to 300 mg of acamprosate. Inactive ingredients in acamprosate calcium delayed-release tablets include: colloidal silicon dioxide, crospovidone, methacrylic acid copolymer dispersion, magnesium silicate, magnesium stearate, microcrystalline cellulose, polyvinyl pyrollidone, propylene glycol, sodium starch glycolate, and talc. Sulfites were used in the synthesis of the drug substance and traces of residual sulfites may be present in the drug product.

12 CLINICAL PHARMACOLOGY

12.1 Mechanism of Action

The mechanism of action of acamprosate in maintenance of alcohol abstinence is not completely understood. Chronic alcohol exposure is hypothesized to alter the normal balance between neuronal excitation and inhibition. In vitro and in vivo studies in animals have provided evidence to suggest acamprosate may interact with glutamate and GABA neurotransmitter systems centrally, and has led to the hypothesis that acamprosate restores this balance.

12.2 Pharmacodynamics

Pharmacodynamic studies have shown that acamprosate calcium reduces alcohol intake in alcohol-dependent animals in a dose-dependent manner and that this effect appears to be specific to alcohol and the mechanisms of alcohol dependence.

Acamprosate calcium has negligible observable central nervous system (CNS) activity in animals outside of its effects on alcohol dependence, exhibiting no anticonvulsant, antidepressant, or anxiolytic activity.

The administration of acamprosate calcium is not associated with the development of tolerance or dependence in animal studies. Acamprosate calcium did not produce any evidence of withdrawal symptoms in patients in clinical trials at therapeutic doses. Post marketing data, collected retrospectively outside the U.S. have provided no evidence of acamprosate calcium abuse or dependence.

Acamprosate calcium is not known to cause alcohol aversion and does not cause a disulfiram-like reaction as a result of ethanol ingestion.

12.3 Pharmacokinetics

Absorption

The absolute bioavailability of acamprosate calcium after oral administration is about 11%. Steady-state plasma concentrations of acamprosate are reached within 5 days of dosing. Steady-state peak plasma concentrations after acamprosate calcium doses of 2 x 333 mg tablets three times daily average 350 ng/mL and occur at 3 to 8 hours post-dose. Coadministration of acamprosate calcium with food decreases bioavailability as measured by Cmax and AUC, by approximately 42% and 23%, respectively. The food effect on absorption is not clinically significant and no adjustment of dose is necessary.

Distribution

The volume of distribution for acamprosate following intravenous administration is estimated to be 72 to 109 liters (approximately 1 L/kg). Plasma protein binding of acamprosate is negligible.

Metabolism

Acamprosate does not undergo metabolism.

Elimination

After oral dosing of 2 x 333 mg of acamprosate calcium, the terminal half-life ranges from approximately 20 to 33 hours. Following oral administration of acamprosate calcium, the major route of excretion is via the kidneys as acamprosate.

Special Populations

Gender: Acamprosate calcium does not exhibit any significant pharmacokinetic differences between male and female subjects.

Age: The pharmacokinetics of acamprosate calcium have not been evaluated in a geriatric population. However, since renal function diminishes in elderly patients and acamprosate is excreted unchanged in urine, acamprosate plasma concentrations are likely to be higher in the elderly population compared to younger adults.

Pediatrics: The pharmacokinetics of acamprosate calcium have not been evaluated in a pediatric population.

Renal Impairment: Peak plasma concentrations after administration of a single dose of 2 x 333 mg acamprosate calcium tablets to patients with moderate or severe renal impairment were about 2-fold and 4-fold higher, respectively, compared to healthy subjects. Similarly, elimination half-life was about 1.8-fold and 2.6-fold longer, respectively, compared to healthy subjects. There is a linear relationship between creatinine clearance values and total apparent plasma clearance, renal clearance and plasma half-life of acamprosate. A dose of 1 x 333 mg acamprosate calcium, three times daily, is recommended in patients with moderate renal impairment (creatinine clearance of 30 to 50 mL/min, [see Use in Specific Populations (8.6)].

Acamprosate calcium is contraindicated in patients with severe renal impairment (creatinine clearance of ≤30 mL/min) [see Dosage and Administration (2.1), Contraindications (4.2), Warnings and Precautions (5.1), and Use in Specific Populations (8.6)].

Hepatic Impairment: Acamprosate is not metabolized by the liver and the pharmacokinetics of acamprosate calcium are not altered in patients with mild to moderate hepatic impairment (groups A and B of the Child-Pugh classification). No adjustment of dosage is recommended in such patients.

Alcohol-dependent subjects: A cross-study comparison of acamprosate calcium at doses of 2 x 333 mg three times daily indicated similar pharmacokinetics between alcohol-dependent subjects and healthy subjects.

Drug-Drug Interactions

Acamprosate had no inducing potential on the cytochrome CYP1A2 and 3A4 systems, and in vitro inhibition studies suggest that acamprosate does not inhibit in vivo metabolism mediated by cytochrome CYP1A2, 2C9, 2C19, 2D6, 2E1, or 3A4. The pharmacokinetics of acamprosate calcium were unaffected when co-administered with alcohol, disulfiram or diazepam. Similarly, the pharmacokinetics of ethanol, diazepam and nordiazepam, imipramine and desipramine, naltrexone and 6-beta naltrexol were unaffected following co-administration with acamprosate calcium. However, co-administration of acamprosate calcium with naltrexone led to a 33% increase in the Cmax and a 25% increase in the AUC of acamprosate. No adjustment of dosage is recommended in such patients.

13 NONCLINICAL TOXICOLOGY

13.1 Carcinogenesis, Mutagenesis, Impairment of Fertility

Dietary administration of acamprosate calcium for 2 years to Sprague-Dawley rats at doses of 25, 100 and 400 mg/kg/day (up to 3 times the maximum recommended human daily (MRHD) oral dose on an AUC basis) and CD-1 mice at doses of 400, 1200 and 3600 mg/kg/day (up to 25 times the MRHD on an AUC basis) showed no evidence of increased tumor incidence.

Acamprosate calcium was negative in all genetic toxicology studies conducted. Acamprosate calcium demonstrated no evidence of genotoxicity in an in vitro bacterial reverse point mutation assay (Ames assay) or an in vitro mammalian cell gene mutation test using

Chinese Hamster Lung V79 cells. No clastogenicity was observed in an in vitro chromosomal aberration assay in human lymphocytes and no chromosomal damage detected in an in vivo mouse micronucleus assay.

Acamprosate calcium had no effect on fertility after treatment for 70 days prior to mating in male rats and for 14 days prior to mating, throughout mating, gestation and lactation in female rats at doses up to 1000 mg/kg/day (approximately 4 times the MRHD oral dose on a mg/m^2 basis). In mice, acamprosate calcium administered orally for 60 days prior to mating and throughout gestation in females at doses up to 2400 mg/kg/day (approximately 5 times the MRHD oral dose on a mg/m^2 basis) had no effect on fertility.

14 CLINICAL STUDIES

The efficacy of acamprosate calcium in the maintenance of abstinence was supported by three clinical studies involving a total of 998 patients who were administered at least one dose of acamprosate calcium or placebo as an adjunct to psychosocial therapy. Each study was a double-blind, placebo-controlled trial in alcohol-dependent patients who had undergone inpatient detoxification and were abstinent from alcohol on the day of randomization. Study durations ranged from 90 days to 360 days. Acamprosate calcium proved superior to placebo in maintaining abstinence, as indicated by a greater percentage of subjects being assessed as continuously abstinent throughout treatment.

In a fourth study, the efficacy of acamprosate calcium was evaluated in alcoholics, including patients with a history of polysubstance abuse and patients who had not undergone detoxification and were not required to be abstinent at baseline. This study failed to demonstrate superiority of acamprosate calcium over placebo.

16 HOW SUPPLIED/STORAGE AND HANDLING

Acamprosate calcium delayed-release tablets, 333 mg are white to off-white, round, biconvex, enteric-coated tablets debossed with ‘435’ on one side and plain on the other side.

Cartons of 30 delayed-release tablets (10 delayed-release tablets each blister pack x 3), NDC 0904-7213-04

WARNING: This Unit Dose package is not child resistant and is Intended for Institutional Use Only. Keep this and all drugs out of the reach of children.

Storage and Handling

Store at 20ºC to 25°C(68° F to 77ºF); excursions permitted to 15ºC to 30ºC (59ºF to 86ºF) [see USP Controlled Room Temperature].

17 PATIENT COUNSELING INFORMATION

17.1 Information for Patients

Physicians are advised to discuss the following issues with patients for whom they prescribe acamprosate calcium.

Renal Impairment

A lower dose is recommended for patients with moderate renal impairment. Acamprosate calcium is contraindicated in patients with severe renal impairment (creatinine clearance of ≤30 mL/min) [see Dosage and Administration (2.1), Contraindications (4.2), Warnings and Precautions (5.1) and Use in Specific Populations (8.6)].

Suicidality and Depression

Families and caregivers of patients being treated with acamprosate calcium should be alerted to the need to monitor patients for the emergence of symptoms of depression or suicidality, and to report such symptoms to the patient's health care provider [see Warnings andPrecautions (5.2)].

Alcohol Withdrawal

Use of acamprosate calcium does not eliminate or diminish withdrawal symptoms [see Warnings and Precautions (5.3)].

Pregnancy and Breast Feeding

- Advise patients to notify their physician if they become pregnant or intend to become pregnant during therapy.
- Advise patients to notify their physician if they are breast-feeding.

Relapse to Drinking

- Advise patients to continue acamprosate calcium therapy as directed, even in the event of relapse and remind them to discuss any renewed drinking with their physicians.
- Advise patients that acamprosate calcium has been shown to help maintain abstinence only when used as a part of a treatment program that includes counseling and support.

Distributed by:

Glenmark Pharmaceuticals Inc., USA

Elmwood Park, NJ 07407

Questions? 1 (888) 721-7115

www.glenmarkpharma-us.com

Packaged and Distributed by:

MAJOR® PHARMACEUTICALS

Indianapolis, IN 46268 USA

Refer to package label for Distributor's NDC Number

May 2025

Package/Label Display Panel

MAJOR®

NDC 0904-7213-04

Unit Dose

Acamprosate Calcium

Delayed-Release

Tablets

333 mg

30 TABLETS (3 x 10)

Rx only